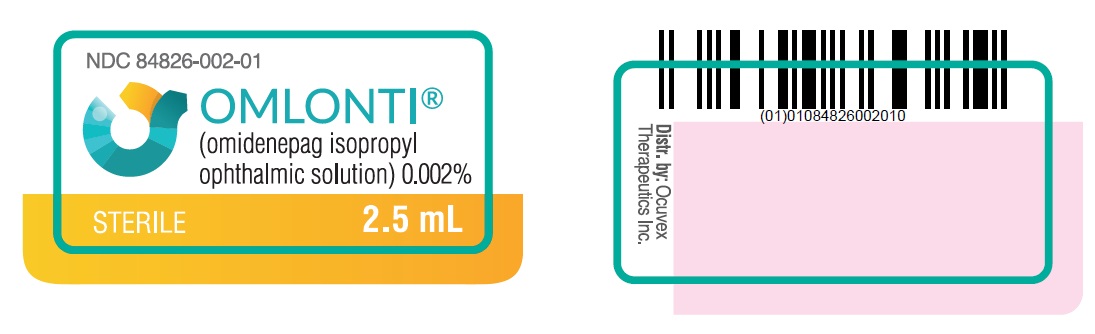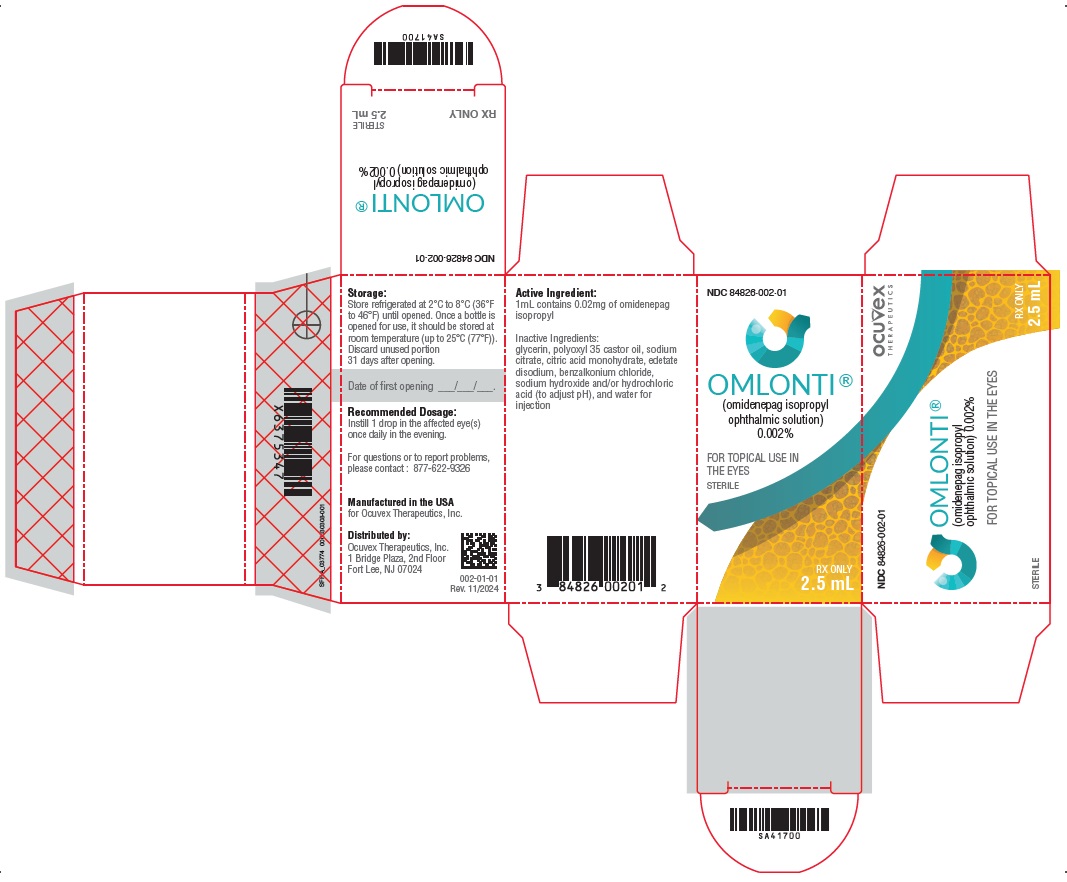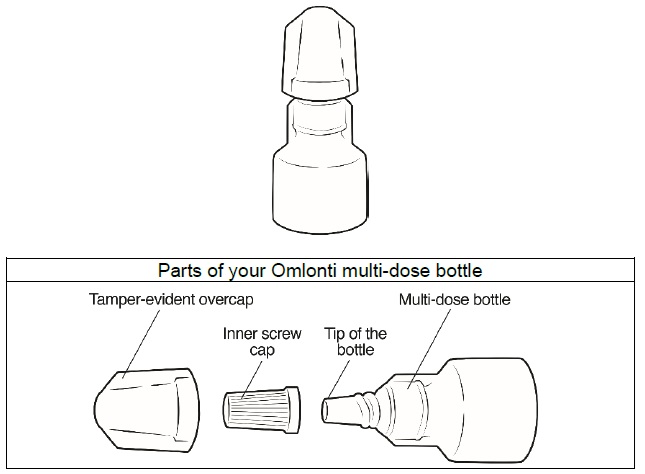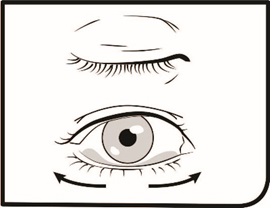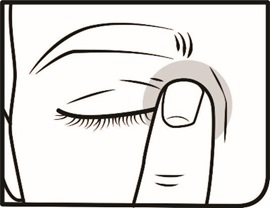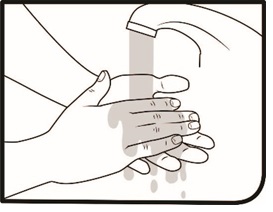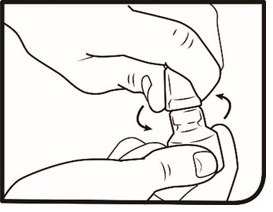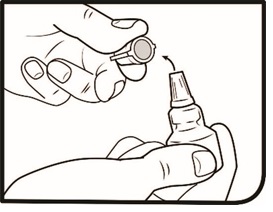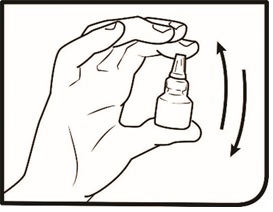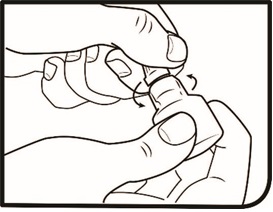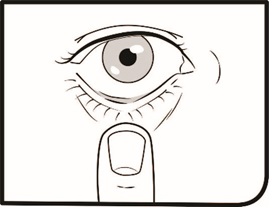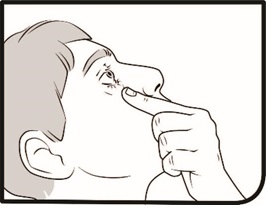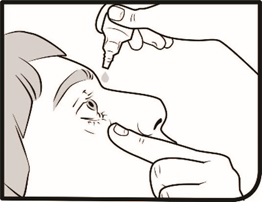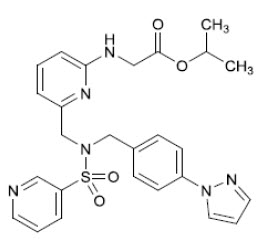 DRUG LABEL: Omlonti
NDC: 84826-002 | Form: SOLUTION/ DROPS
Manufacturer: Ocuvex Therapeutics, Inc.
Category: prescription | Type: HUMAN PRESCRIPTION DRUG LABEL
Date: 20250421

ACTIVE INGREDIENTS: OMIDENEPAG ISOPROPYL 0.02 mg/1 mL
INACTIVE INGREDIENTS: SODIUM HYDROXIDE; HYDROCHLORIC ACID; WATER

HIGHLIGHTS OF PRESCRIBING INFORMATION

These highlights do not include all the information needed to use OMLONTI®safely and effectively. See full prescribing information for OMLONTI®.
OMLONTI®(omidenepag isopropyl ophthalmic solution) 0.002%, for topical ophthalmic use
Initial U.S. Approval: 2022

1 INDICATIONS AND USAGE

Omlonti (omidenepag isopropyl ophthalmic solution) 0.002%, is a relatively selective prostaglandin E2 (EP2) receptor agonist, indicated for the reduction of elevated intraocular pressure (IOP) in patients with open-angle glaucoma or ocular hypertension. (1)

2 DOSAGE AND ADMINISTRATION

The recommended dosage is one drop in the affected eye(s) once daily in the evening. (2.1)

3 DOSAGE FORMS AND STRENGTHS

Ophthalmic solution containing 0.002% (0.02 mg/mL) of omidenepag isopropyl. (3)

4 CONTRAINDICATIONS

None (4)

5 WARNINGS AND PRECAUTIONS

- Pigmentation (5.1)
- Eyelash changes (5.2)
- Ocular Inflammation (5.3)
- Macular Edema (5.4)

6 ADVERSE REACTIONS

The most common adverse reactions with incidence ≥ 1% are conjunctival hyperemia (9%), photophobia (5%), vision blurred (4%), dry eye (3%), instillation site pain (3%), eye pain (2%), ocular hyperemia (2%), punctate keratitis (2%), headache (2%), eye irritation (1%), and visual impairment (1%). (6.1)

To report SUSPECTED ADVERSE REACTIONS, contact Ocuvex at 1-877-622-9326 or FDA at 1-800-FDA-1088 or www.fda.gov/medwatch.

FULL PRESCRIBING INFORMATION

1 INDICATIONS AND USAGE

Omlonti (omidenepag isopropyl ophthalmic solution) 0.002%, is indicated for the reduction of elevated intraocular pressure (IOP) in patients with open-angle glaucoma or ocular hypertension.

2 DOSAGE AND ADMINISTRATION

2.1 Recommended Dosage

The recommended dosage is one drop in the affected eye(s) once daily in the evening.

2.2 Administration Instructions

Gently shake the bottle prior to administration. If more than one topical ophthalmic drug is being used, the drugs should be administered at least five (5) minutes apart. Contact lenses should be removed prior to the administration of Omlonti, and may be reinserted 15 minutes after administration [see Patient Counseling Information (17)].

3 DOSAGE FORMS AND STRENGTHS

Omidenepag isopropyl ophthalmic solution: 0.002% (0.02 mg/mL)

4 CONTRAINDICATIONS

None.

5 WARNINGS AND PRECAUTIONS

5.1 Pigmentation

Omlonti (omidenepag isopropyl ophthalmic solution) 0.002%, is a prodrug of omidenepag, a relatively selective EP2 receptor agonist. Pigmentation is expected to increase as long as omidenepag isopropyl ophthalmic solution is administered. The pigmentation change is due to increased melanin content in the melanocytes rather than to an increase in the number of melanocytes. After discontinuation of Omlonti, pigmentation of the iris is likely to be permanent, while pigmentation of the periorbital tissue and eyelash changes are likely to be reversible in most patients. Patients who receive prostaglandin analogs, including Omlonti, should be informed of the possibility of increased pigmentation, including permanent changes. The long-term effects of increased pigmentation are not known.

Iris color change may not be noticeable for several months to years. Typically, the brown pigmentation around the pupil spreads concentrically towards the periphery of the iris and the entire iris or parts of the iris become more brownish. Neither nevi nor freckles of the iris appear to be affected by treatment. While treatment with Omlonti (omidenepag isopropyl ophthalmic solution), 0.002% can be continued in patients who develop noticeably increased iris pigmentation, these patients should be examined regularly [see Patient Counseling Information (17)] .

5.2 Eyelash Changes

Omlonti may gradually change eyelashes and vellus hair in the treated eye. These changes include increased length, thickness, and the number of lashes or hairs. Eyelash changes are usually reversible upon discontinuation of treatment.

5.3 Ocular Inflammation

Ocular inflammation has been reported in patients taking Omlonti. Omlonti should be used with caution in patients with active ocular inflammation, including iritis/uveitis.

5.4 Macular Edema

Macular edema, including cystoid macular edema, has been reported during clinical trials in patients with pseudophakia receiving Omlonti. Omlonti should be used with caution in aphakic patients, in pseudophakic patients, or in patients with known risk factors for macular edema.

5.5 Risk of Contamination and Potential Injury to the Eye

Advise patients to avoid touching the tip of the bottle to the eye or any surface, as this may contaminate the solution. Advise patients to not touch the tip to their eye to avoid the potential for injury to the eye.

6 ADVERSE REACTIONS

The following clinically significant adverse reactions are described elsewhere in the labeling:

- Pigmentation [see Warnings and Precautions (5.1)]
- Eyelash Changes [see Warnings and Precautions (5.2)]
- Ocular Inflammation [see Warnings and Precautions (5.3)]
- Macular Edema [see Warnings and Precautions (5.4)]

6.1 Clinical Trials Experience

Because clinical trials are conducted under widely varying conditions, adverse reaction rates observed in the clinical trials of a drug cannot be directly compared to rates in the clinical trials of another drug and may not reflect the rates observed in practice.

The data described below reflect exposure to Omlonti in 600 patients for up to 3 months .The most common adverse reactions with incidence ≥ 1% are conjunctival hyperemia (9%), photophobia (5%), vision blurred (4%), dry eye (3%), instillation site pain (3%), eye pain (2%), ocular hyperemia (2%), punctate keratitis (2%), headache (2%), eye irritation (1%), and visual impairment (1%).

8 USE IN SPECIFIC POPULATIONS

8.1 Pregnancy

Risk Summary

There are no available data on the use of Omlonti in pregnant women. In animal reproduction studies, subcutaneous administration of omidenepag isopropyl to pregnant rabbits throughout the period of organogenesis produced fetal skeletal anomalies at a dose of 24 times the clinical dose, based on estimated plasma Cmax. Omidenepag isopropyl was not teratogenic in rats when administered subcutaneously at 1 mg/kg/day, 2,452 times the clinical dose, based on estimated plasma Cmax (see Data) .

Data

Animal Data

An embryofetal development study was conducted in pregnant rabbits administered omidenepag isopropyl once daily by subcutaneous injection at 0.008, 0.08, or 0.8 mg/kg/day from gestation Day 6 to 18, a period which covers implantation and the period of organogenesis in rabbits. Fetal skeletal anomalies (thoracic misaligned centrum and hemivertebra, fused sternebra, absent rib) were observed at 0.008 mg/kg/day (24 times the maximum recommended human ocular dose [MRHOD], based on estimated plasma Cmax). Additional fetal skeletal anomalies were observed at 0.08 mg/kg (absent thoracic arch, fused rib) and 0.8 mg/kg (misaligned and misshapen cervical vertebrae), corresponding to 256 times and 3,696 times the MRHOD based on estimated plasma Cmax, respectively. Increases in preimplantation loss and post-implantation loss were observed at 0.8 mg/kg/day. The rabbit maternal, No Observed Adverse Effect Level [NOAEL] was 0.8 mg/kg/day.

An embryofetal development study was conducted in pregnant rats administered omidenepag isopropyl once daily by subcutaneous injection at 0.01, 0.1, or 1 mg/kg/day from gestation Day 6 to 17, to target the period of organogenesis. Omidenepag isopropyl was not found to have any effect on embryo-fetal development in rats at up to 1 mg/kg/day (2,452 times the MRHOD based on estimated plasma Cmax). The rat maternal NOAEL was 1 mg/kg/day. In a pre/postnatal development study, treatment of pregnant rats with omidenepag isopropyl subcutaneously from gestation day 6 to lactation day 20 at 0.01, 0.1, or 1 mg/kg/day resulted in no adverse effects. The NOAEL for pre- and postnatal development was 1 mg/kg/day (2,452 times the MRHOD based on estimated plasma Cmax).

8.2 Lactation

Risk Summary

There are no data on the presence of Omlonti in human milk, the effects on the breastfed infant, or the effects on milk production. However, systemic exposure to omidenepag following topical ocular administration is low [see Clinical Pharmacology (12.3)], and it is not known whether measurable levels of omidenepag would be present in maternal milk following topical ocular administration. The developmental and health benefits of breastfeeding should be considered along with the mother's clinical need for Omlonti and any unknown potential adverse effects on the breast-fed child from Omlonti.

8.3 Females and Males of Reproductive Potential

Infertility

There are no data on the effects of Omlonti on human fertility. No impairment of fertility has been reported in animals receiving omidenepag isopropyl subcutaneously at doses up to 2,452 times the clinical dose based on estimated plasma Cmax [see Nonclinical Toxicology (13.1)] .

8.4 Pediatric Use

The safety and effectiveness of Omlonti have not been established in pediatric patients.

8.5 Geriatric Use

No overall differences in safety or effectiveness have been observed between elderly and other adult patients.

11 DESCRIPTION

Omlonti (omidenepag isopropyl ophthalmic solution) 0.002%, contains the prodrug form of the active omidenepag, a relatively selective prostaglandin EP2 receptor agonist with ocular hypotensive activity. Omidenepag isopropyl is a white to light brown crystal or crystalline powder and practically insoluble in water. Omidenepag isopropyl's chemical name is Glycine, N-[6-[[[[4-(1H-pyrazol-1-yl)phenyl]methyl](3-pyridinylsulfonyl)amino]methyl]-2-pyridinyl]-, 1-methylethyl ester and has the following structure:

Structural Formula

Formula of the free base: C26H28N6O4S. Molecular weight: 520.61

Omlonti appears as a clear, colorless solution. It is supplied as a sterile, isotonic, buffered aqueous solution of omidenepag isopropyl with a target pH of 5.8 and an osmolality of approximately 285 mOsmol/kg.

Each mL of Omlonti contains: Active: 0.02 mg of omidenepag isopropyl.

Preservative: 0.005% benzalkonium chloride.

Inactive ingredients: glycerin, polyoxyl 35 castor oil, sodium citrate, citric acid monohydrate, edetate disodium, sodium hydroxide and/or hydrochloric acid (to adjust pH), and water for injection.

12 CLINICAL PHARMACOLOGY

12.1 Mechanism of Action

Omidenepag is a relatively selective EP2 receptor agonist which decreases intraocular pressure (IOP). The exact mechanism of action is unknown at this time. Elevated IOP represents a major risk factor for glaucomatous field loss. The higher the level of IOP, the greater the likelihood of optic nerve damage and visual field loss.

12.3 Pharmacokinetics

Absorption

Omlonti is absorbed through the cornea where prodrug omidenepag isopropyl is hydrolyzed to become biologically active metabolite, omidenepag. After once daily ocular administration of one drop of omidenepag isopropyl 0.0025% eye drops to both eyes in humans for 7 days, plasma concentrations of omidenepag reached Cmaxat 10-15 minutes. Systemic exposure was similar between days 1 and 7, indicating no systemic accumulation.

Elimination

Metabolism

After topical ocular administration, omidenepag isopropyl is rapidly metabolized in the eye to omidenepag (active moiety) by carboxylesterase-1. The pharmacologically active form, omidenepag is further metabolized by liver through oxidation, N-dealkylation, glucuronidation, sulfate conjugation or taurine conjugation.

Excretion

In rats, 0.03%^14C-Omlonti was instilled in both eyes as a single dose (5 mcL/eye, 3 mcg/animal). By 168 hours after ocular instillation, 89% of the administered radioactive dose had been excreted. Specifically, 83% and 4% of the administered radioactive dose were excreted in the feces and urine, respectively, and radioactivity in expired air was below the lower limit of quantitation.

13 NONCLINICAL TOXICOLOGY

13.1 Carcinogenesis, Mutagenesis, Impairment of Fertility

Carcinogenesis

Lifetime rodent studies have not been performed to evaluate the carcinogenic potential of omidenepag isopropyl or omidenepag.

In rats dosed by subcutaneous injection daily for 26 weeks, nephroblastoma and a spermatic cord tumor were found at 0.003 mg/kg/day (33 times the RHOD based on the estimated area under the curve [AUC]). Mammary adenocarcinoma and pituitary pars distalis adenomas were observed at 0.03 mg/kg/day (319 fold the RHOD based on the estimated AUC).

Mutagenesis

Omidenepag was not mutagenic in the bacterial reverse mutation (Ames) test and the in vivomouse micronucleus test. Omidenepag isopropyl was positive (mutagenic and clastogenic) without metabolic activation in the in vitromouse lymphoma forward mutation assay. [see Clinical Pharmacology (12.3)] .

Impairment of Fertility

In a rat fertility and early embryonic development study, daily subcutaneous doses of omidenepag isopropyl did not affect male or female fertility at doses up to 1 mg/kg/day (2,452 times the MRHOD based on estimated plasma Cmax).

The rabbit embryofetal development study administered omidenepag isopropyl to pregnant rabbits beginning on gestation day 6, covering the period of implantation [see Use in Specific Populations (8.1)] . Preimplantation losses were observed at 0.8 mg/kg/day (3,696 times the MRHOD based on estimated plasma Cmax). The NOAEL for rabbit preimplantation loss was 0.08 mg/kg/day (256 times the MHROD based on estimated plasma Cmax) [see Use in Specific Populations (8.1)] .

13.2 Animal Toxicology and/or Pharmacology

Nasal cavity respiratory epithelium metaplasia was observed in cynomolgus monkeys receiving unilateral topical ocular instillations of omidenepag isopropyl at 0.003% (0.9 mcg/eye) [1.07 fold the MRHOD, based on ocular dose comparison]. In a 13-week monkey study, the 0.9 mcg/eye dose was associated with nasal cavity respiratory epithelial metaplasia, and increased nasal cavity goblet cell respiratory epithelium mucosa. In a 39-week monkey study, the 0.9 mcg/eye dose was associated with increased incidence and severity of nasal cavity respiratory epithelium metaplasia. These findings were present in both the treated side and untreated contralateral side, and they were also observed in the vehicle group [see Adverse Reactions (6)] .

14 CLINICAL STUDIES

Omlonti was evaluated in three randomized and controlled clinical trials in subjects with open-angle glaucoma or ocular hypertension with average baseline IOP of 24-26 mm Hg. The double-masked treatment duration was 3 months in all 3 studies. The third study included a 9-month open-label treatment period following the 3-month double-masked treatment period.

In the three studies, IOP reductions were observed for all treatment arms. In the Omlonti arm, the reduction in IOP ranged from 5-7 mm Hg across all three studies. The corresponding reductions for the timolol and latanoprost arms were 5-7 mm Hg and 6-8 mm Hg, respectively.

16 HOW SUPPLIED/STORAGE AND HANDLING

Omlonti (omidenepag isopropyl ophthalmic solution) 0.002%, is supplied as a 2.5 mL sterile solution in 5 mL white low density polyethylene bottles with linear low density polyethylene dropper tips, high density polyethylene screw caps and tamper-evident low density polyethylene overcaps.

Package of 1 bottle, NDC 84826-002-01

Multi-pack of 3 bottles, NDC 84826-002-03

STORAGE AND HANDLING

Storage: Store unopened bottle (s) in the refrigerator at 2°C to 8°C (36°F to 46°F). Once a bottle is opened for use, it can be stored for up to 31 days at up to 30°C (86°F).

17 PATIENT COUNSELING INFORMATION

Advise the patient to read the FDA-approved patient labeling (Instructions for Use).

Potential for Pigmentation

Patients should be advised about the potential for increased brown pigmentation of the iris, which may be permanent. Patients should also be informed about the possibility of eyelid skin darkening, which is usually reversible after discontinuation of Omlonti.

Potential for Eyelash Changes

Patients should also be informed of the possibility of eyelash and vellus hair changes in the treated eye during treatment with Omlonti. These changes may result in a disparity between eyes in length, thickness, pigmentation, number of eyelashes or vellus hairs, and/or direction of eyelash growth. Eyelash changes are usually reversible upon discontinuation of treatment.

Handling the Container

Advise patients to avoid touching the tip of the bottle to the eye or any surface, as this may contaminate the solution. Advise patients to not touch the tip to their eye to avoid the potential for injury to the eye. The product should be refrigerated before opening, and once it is opened, it can be stored at room temperature for up to 31 days . [see How Supplied/Storage and Handling (16)] .

When to Seek Physician Advice

Advise patients that if they develop a new ocular condition (e.g., trauma, infection, or inflammation), experience a sudden decrease in visual acuity, have ocular surgery, or develop any ocular reactions, particularly conjunctivitis and eyelid reactions, they should immediately seek their physician's advice concerning the continued use of Omlonti.

Use with Contact Lenses

Contact lenses should be removed prior to administration of the solution. Lenses may be reinserted 15 minutes after administration.

Use with Other Ophthalmic Drugs

Advise patients that if more than one topical ophthalmic drug is being used, the drugs should be administered at least five (5) minutes apart [see Dosage and Administration (2)] .

Manufactured for:

Ocuvex Therapeutics, Inc
1 Bridge Plaza, 2ndFloor
Fort Lee, NJ 07024

PI-002-01
Rev 10/2024

PATIENT INFORMATION

INSTRUCTIONS FOR USE

OMLONTI® [om lon’tee]

(omidenepag isopropyl ophthalmic solution) 0.002%

for topical ophthalmic use

Read this Instructions for Use before you start using Omlonti and each time you get refills. There may be new and updated information. This leaflet does not take the place of talking to your healthcare provider about your medical condition or your treatment.

Important information you need to know before using Omlonti

- Omlonti is for use in the eye.
- Use Omlonti exactly as your healthcare provider tells you to use it.
- After you remove the Omlonti multi-dose bottle from the carton, make sure the tamper-evident overcap is not broken. If the tamper-evident overcap is broken, Omlonti may not be safe for you to use.
- If you use Omlonti with other eye medicines, you should wait at least 5 minutes between using Omlonti and the other medicines.
- If you wear contact lenses, remove your contact lenses before using Omlonti. You should wait 15 minutes after using Omlonti before placing your contact lenses back in your eye.
- Call your healthcare provider right away if you develop new eye problems including: an eye injury, eye infection, eye pain, light sensitivity, blurry vision, decreased vision, swelling and redness of the eye, problems with your eyelids, changes in the appearance of your eyes, headache, or eye surgery.
- If you develop blurred vision or light sensitivity after using Omlonti, do notdrive or operate heavy machinery until the symptoms disappear.
- Omlonti can cause color changes in your iris and eyelid and may change the length and color of your eyelashes.

Using Omlonti

Follow Step 1to Step 11each time you use Omlonti. Ask your healthcare provider for help if you do not understand how to use Omlonti.

Step 1. Wash your hands thoroughly with soap and water. If you cannot wash your hands, you can clean your hands using hand sanitizer.

Step 2. Turn the tamper-evident overcap to the left to open the multi-dose bottle.

Step 3. Remove the tamper-evident overcap and throw it away.

Step 4. Gently shake the bottle.

Step 5. Turn the inner screw cap to the left to remove it. Do not throw the inner screw cap away.

Step 6. Pull down your lower eyelid with a clean finger. The medicine will go into the space between your lower eyelid and your eye.

Step 7. Tilt your head back and look up.

Step 8. Gently squeeze the multi-dose bottle to release 1 drop of the medicine in your eye. Do not let the tip of the multi-dose bottle touch your eye or any other surfaces. If a drop misses your eye, try again.

Step 9. Blink a few times so that the medicine spreads across your eye.

Step 10. After using Omlonti, gently close your eyelid and press the corner of your eye closest to your nose for 2 minutes.

Step 11. Repeat Step 6 to Step 10 for your other eye if you need to use drops in both eyes.

Storing Omlonti

- Store unopened Omlonti in the refrigerator between 36°F to 46°F (2°C to 8°C).
- After opening, store Omlonti up to 31 days at room temperature between 68°F to 86°F (20° to 30°C).
- Do not use Omlonti if the expiration date (EXP YYYY-MM) on the outer carton and multi-dose bottle have passed. The expiration date is the last day of that month.
- After removing the tamper-evident overcap, keep the multi-dose bottle closed with the inner screw cap on to avoid contamination.
- Keep Omlonti and all medicines out of the reach of children.

Additional Information

- If you have questions about Omlonti, talk to your healthcare provider, or call Ocuvex Therapeutics Medical Information: 1-877-622-9326.

Manufactured for:

Ocuvex Therapeutics, Inc
1 Bridge Plaza, 2ndFloor
Fort Lee, NJ 07024

This Instructions for Use has been approved by the U.S. Food and Drug Administration.

Approved: 09/2022

PIL-002-01 Rev: 10/2024

PRINCIPAL DISPLAY PANEL - 2.5 mL Bottle Label

NDC 84826-002-01

Ocuvex

OMLONTI®
(omidenepag isopropyl
ophthalmic solution) 0.002%

FOR TOPICAL USE
IN THE EYES

STERILE

RX ONLY

2.5 mL

PRINCIPAL DISPLAY PANEL - 2.5 mL Carton Label

NDC 84826-002-01

Ocuvex

OMLONTI®
(omidenepag isopropyl
ophthalmic solution) 0.002%

FOR TOPICAL USE
IN THE EYES

STERILE

RX ONLY

2.5 mL